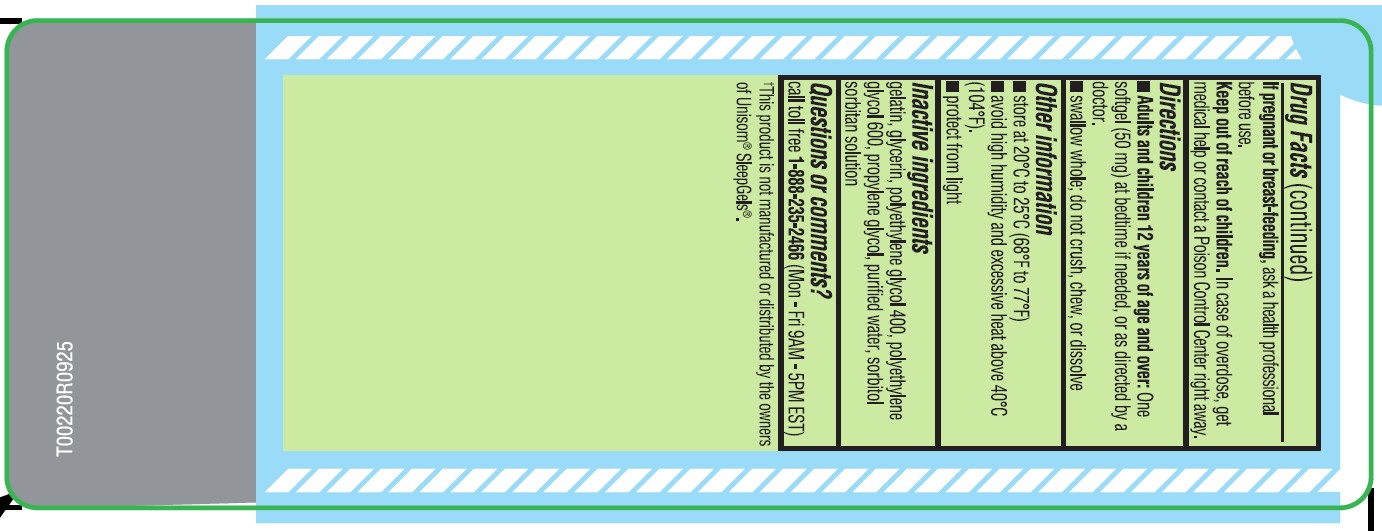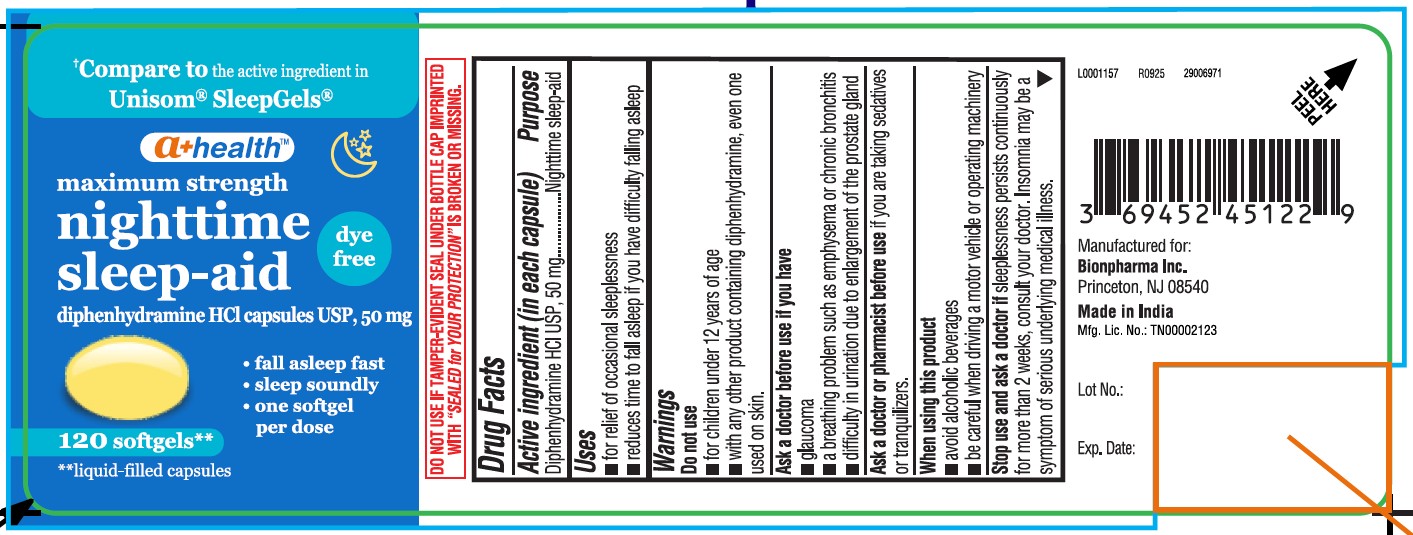 DRUG LABEL: Nighttime Sleep-Aid
NDC: 69452-451 | Form: CAPSULE, LIQUID FILLED
Manufacturer: BIONPHARMA INC.
Category: otc | Type: HUMAN OTC DRUG LABEL
Date: 20251201

ACTIVE INGREDIENTS: DIPHENHYDRAMINE HYDROCHLORIDE 50 mg/1 1
INACTIVE INGREDIENTS: POLYETHYLENE GLYCOL 600; SORBITAN; GELATIN; POLYETHYLENE GLYCOL 400; WATER; GLYCERIN; PROPYLENE GLYCOL; SORBITOL

Diphenhydramine HCl 50mg, A+ Health, Made in India, dye free

Active ingredient (in each capsule)

Diphenhydramine HCl 50 mg

Purpose

Nighttime sleep-aid

Uses

- For relief of occasional sleeplessness
- reduces time to fall asleep if you have difficulty falling asleep

Warnings

Do not use

- for children under 12 years of age
- with any product containing diphenhydramine, even one used on skin.

Ask a doctor before use if you have

- glaucoma
- a breathing problem such as emphysema or chronic bronchitis
- difficulty in urination due to enlargement of the prostate gland

Ask a doctor or pharmacist before use

if you are taking sedatives or tranquilizers.

When using this product

- avoid alcoholic beverages
- be careful when driving a motor vehicle or operating machinery

Stop use and ask a doctor if

sleeplessness persists continuosly for more than 2 weeks, consult your doctor.

Insomnia may be a symptom of serious underlying medical illness.

If pregnant or breast- feeding,

ask a health professional before use.

Keep out of reach of children.

In case of overdose, get medical help or contact a Poison Control Centre right away.

Directions

- Adults and children 12 years of age and over:One softgel (50 mg) at bedtime if needed, or as directed by a doctor.
- swallow whole; do not crush, chew, or dissolve

Other information

- store at 20oC to 25oC (68oF to 77oF)
- avoid high humidity and excessive heat above 40oC (104oF).
- protect from light

Inactive ingredients

gelatin, glycerin, polyethylene glycol 400, polyethylene glycol 600, propylene glycol, purified water, sorbitol sorbitan solution

Questions or comments?

1-888-235-2466(Mon-Fri 9AM-5PM EST)

†This product is not manufactured or distributed by the owners of Unisom® SleepGels®.

DO NOT USE IF TAMPER-EVIDENT SEAL UNDER BOTTLE CAP IMPRINTED WITH “SEALED for YOUR PROTECTION” IS BROKEN OR MISSING.

Manufactured for:

Bionpharma Inc.

Princeton, NJ 08540

Made in India

Mfg. Lic. No.: TN00002123

L0001157

R0925

29006971

Lot No.:

Exp. Date:

120's count

†Compare to the active ingredient in Unisom® SleepGels®

a+ healthTM

maximum strength

nighttime

sleep-aid

dye

free

diphenhydramine HCl capsules USP, 50 mg

• fall asleep fast
• sleep soundly
• one softgel

per dose

120 softgels**

**liquid-filled capsules